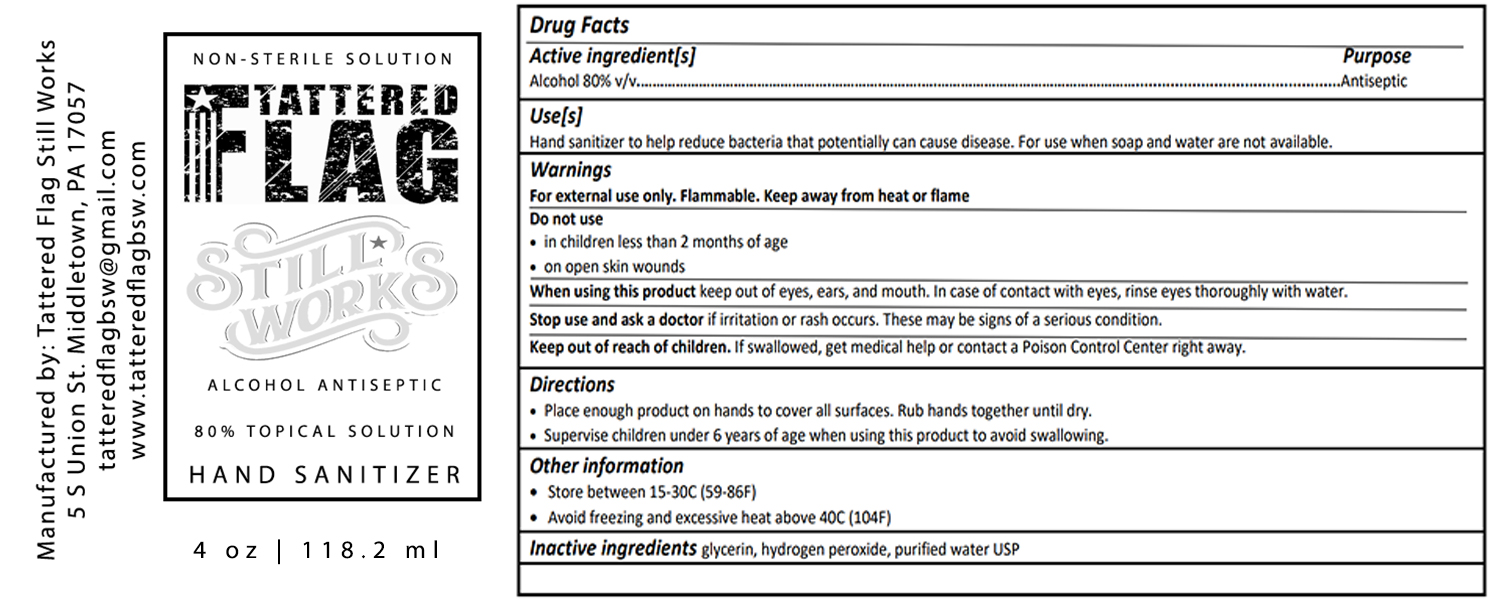 DRUG LABEL: Hand Sanitizer
NDC: 74070-100 | Form: LIQUID
Manufacturer: Tattered Flag Still Works
Category: otc | Type: HUMAN OTC DRUG LABEL
Date: 20200325

ACTIVE INGREDIENTS: ALCOHOL 80 mL/100 mL
INACTIVE INGREDIENTS: HYDROGEN PEROXIDE 3 mL/100 mL

ACTIVE INGREDIENT SECTION

ASK DOCTOR SECTION

ASK DOCTOR/PHARMASIST SECTION

DO NOT USE SECTION

KEEP OUT OF REACH OF CHILDREN SECTION

PREGNANCY OR BREAST FEEDING SECTION

PURPOSE SECTION

QUESTIONS SECTION

STOP USE SECTION

WHEN USING SECTION

DOSAGE AND ADMINISTRATION

DSOAGE & ADMINITRATION SECTION

Warnings Section

INDICATIONS AND USAGE SECTION

INACTIVE INGREDIENTS SECTION